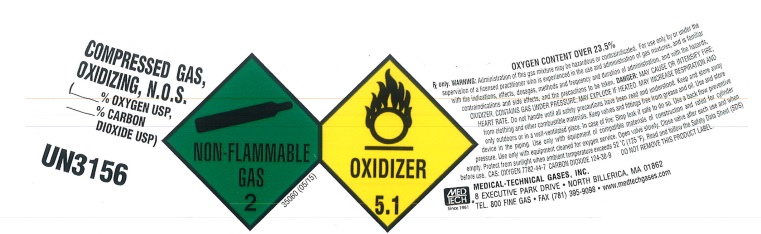 DRUG LABEL: Oxygen Carbon Dioxide
NDC: 10736-204 | Form: GAS
Manufacturer: MEDICAL-TECHNICAL GASES, INC.
Category: prescription | Type: HUMAN PRESCRIPTION DRUG LABEL
Date: 20251125

ACTIVE INGREDIENTS: OXYGEN 950 mL/1 L
INACTIVE INGREDIENTS: CARBON DIOXIDE 50 mL/1 L

CO2/O2 Mix - COMPRESSED GAS, OXIDIZING, N.O.S.- oxygen, carbon dioxide gas

PACKAGE LABEL

O2 CO2

COMPRESSED GAS, OXIDIZING, N.O.S (% OXYGEN USP, % CARBON DIOXIDE USP)

UN3156

OXYGEN CONTENT OVER 23.5%

Rx only. WARNING: Administration of this gas mixture may be hazardous or contraindicated. For use only by or under the supervision of a licensed practitioner who is experienced in the use and administration of gas mixtures, and is familiar with the indications, effects, dosages, methods and frequency and duration of administration, and with the hazards, contraindications and side effects, and the precautions to be taken. DANGER: MAY CAUSE OR INTENSIFY FIRE; OXIDIZER. CONTAINS GAS UNDER PRESSURE; MAY EXPLODE IF HEATED. MAY INCREASE RESPIRATION AND HEART RATE. Do not handle until all safety precautions have been read and understood. Keep and store away from clothing and other combustible materials. Keep valves and fittings free from grease and oil. Use and store only outdoors or in a well-ventilated place. In case of fire: Stop leak if safe to do so. Use a back flow preventive device in the piping. Use only with equipment of compatible materials of construction and rated for cylinder pressure. Use only with equipment cleaned for oxygen service. Open valve slowly. Close valve after each use and when empty. Protect from sunlight when ambient temperature exceeds 52 C (125 F). Read and follow the Safety Data Sheet (SDS) before use. CAS: OXYGEN 7782-44-7 CARBON DIOXIDE 124-38-9 DO NOT REMOVE THIS PRODUCT LABEL.

MEDTECH Since 1961

MEDICAL-TECHNICAL GASES, INC.

8 EXECUTIVE PARK DRIVE NORTH BILLERICA, MA 01862

TEL. 800 FINE GAS FAX (781) 395-9098 www.medtechgases.com